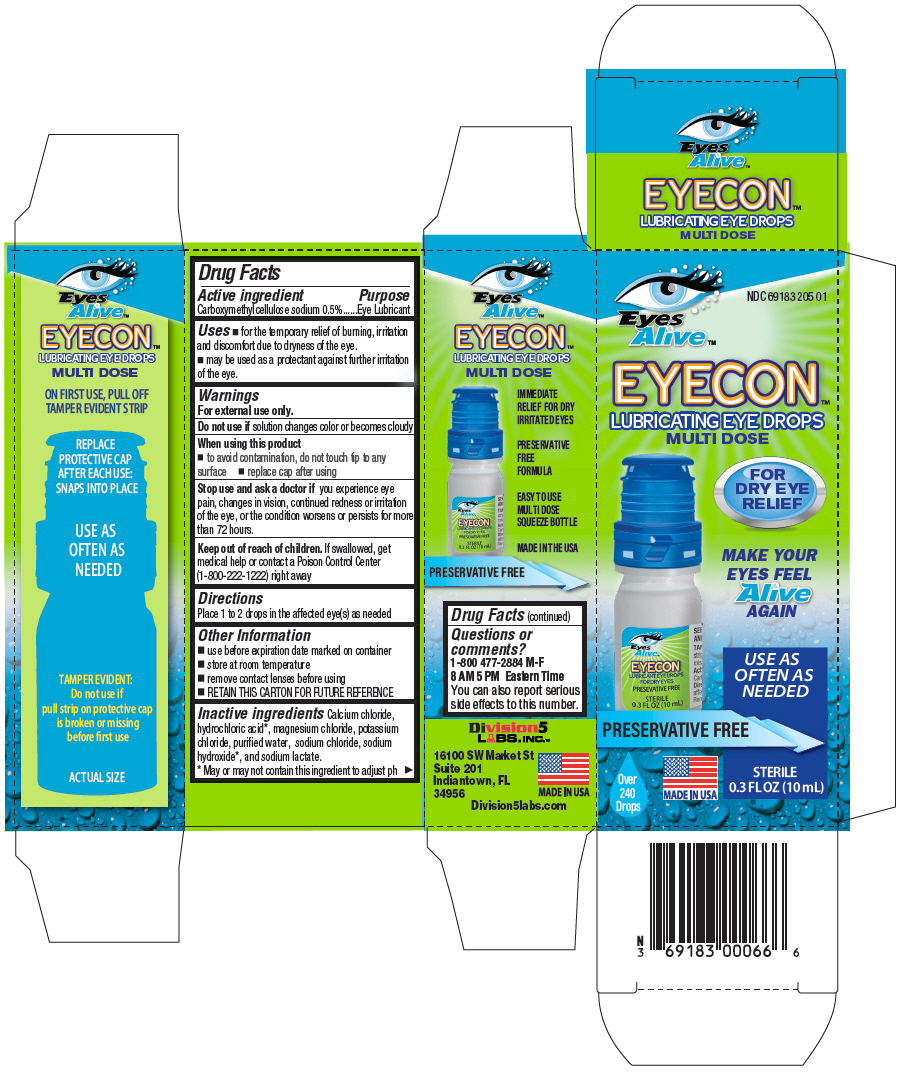 DRUG LABEL: Eyes Alive EYECON
NDC: 69183-205 | Form: LIQUID
Manufacturer: DIVISION 5 LABS, INC.
Category: otc | Type: HUMAN OTC DRUG LABEL
Date: 20191119

ACTIVE INGREDIENTS: CARBOXYMETHYLCELLULOSE SODIUM, UNSPECIFIED FORM 5 mg/1 mL
INACTIVE INGREDIENTS: CALCIUM CHLORIDE; HYDROCHLORIC ACID; MAGNESIUM CHLORIDE; POTASSIUM CHLORIDE; WATER; SODIUM CHLORIDE; SODIUM HYDROXIDE; SODIUM LACTATE

Eyes Alive™ EYECON™
Lubricating

Drug Facts

Active ingredient

Carboxymethylcellulose sodium 0.5%

Purpose

Eye Lubricant

Uses

- for the temporary relief of burning, irritation and discomfort due to dryness of the eye.
- may be used as a protectant against further irritation of the eye.

Warnings

For external use only.

Do not use if solution changes color or becomes cloudy

When using this product

- to avoid contamination, do not touch tip to any surface
- replace cap after using

Stop use and ask a doctor if you experience eye pain, changes in vision, continued redness or irritation of the eye, or the condition worsens or persists for more than 72 hours.

Keep out of reach of children. If swallowed, get medical help or contact a Poison Control Center (1-800-222-1222) right away

Directions

Place 1 to 2 drops in the affected eye(s) as needed

Other Information

- use before expiration date marked on container
- store at room temperature
- remove contact lenses before using
- RETAIN THIS CARTON FOR FUTURE REFERENCE

Inactive ingredients

Calcium chloride, hydrochloric acid [May or may not contain this ingredient to adjust ph] , magnesium chloride, potassium chloride, purified water, sodium chloride, sodium hydroxide, and sodium lactate.

Questions or comments?

1-800 477-2884 M-F 8 AM 5 PM Eastern Time

You can also report serious side effects to this number.

PRINCIPAL DISPLAY PANEL - 10 mL Bottle Carton

NDC 69183 205 01

Eyes
Alive™

EYECON™
LUBRICATING EYE DROPS
MULTI DOSE

FOR
DRY EYE
RELIEF

MAKE YOUR
EYES FEEL
Alive
AGAIN

USE AS
OFTEN AS
NEEDED

PRESERVATIVE FREE

STERILE
0.3 FL OZ (10 mL)

Over
240
Drops

MADE IN USA